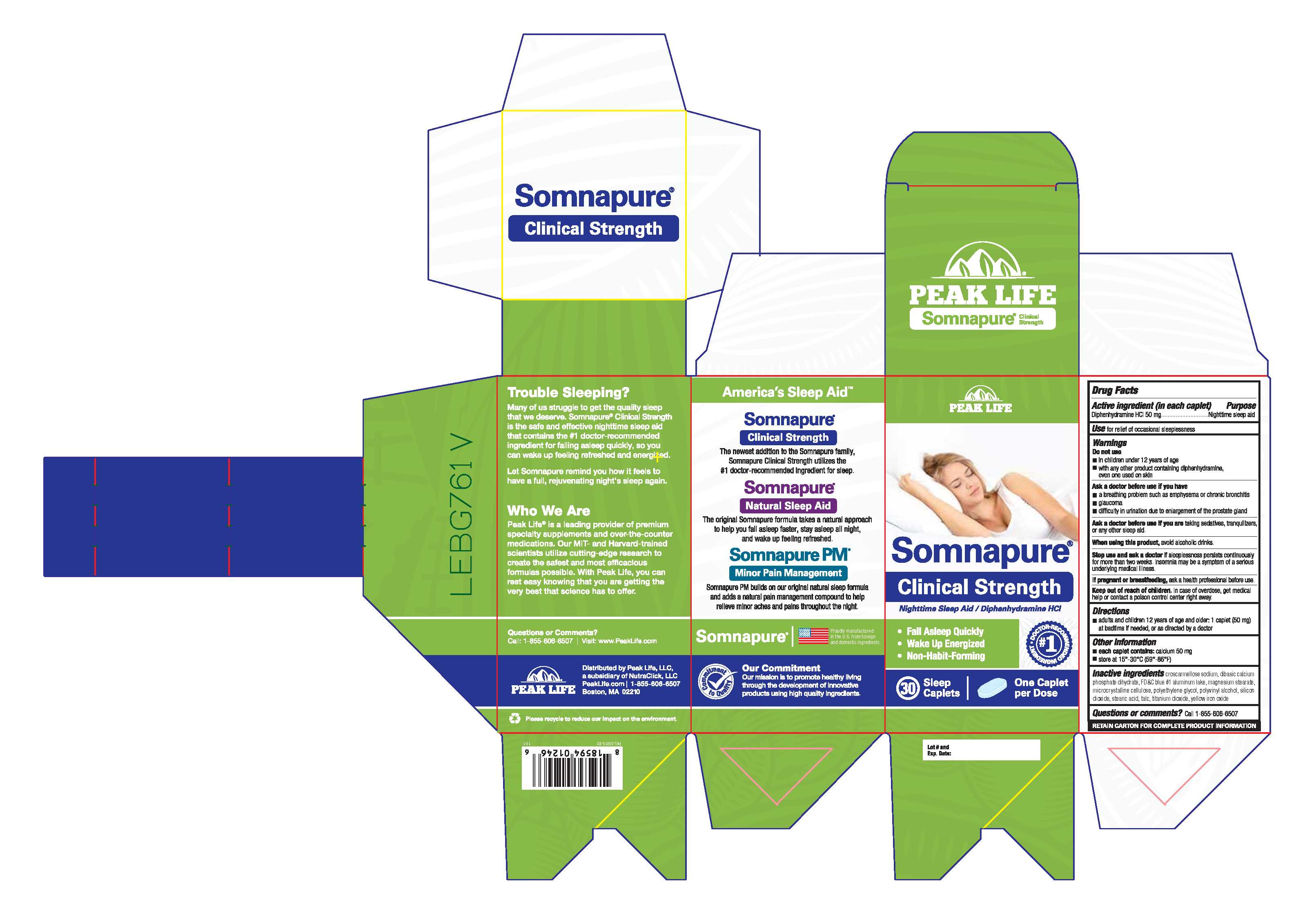 DRUG LABEL: Somnapure
NDC: 69721-003 | Form: TABLET, COATED
Manufacturer: NutraClick, LLC
Category: otc | Type: HUMAN OTC DRUG LABEL
Date: 20180320

ACTIVE INGREDIENTS: DIPHENHYDRAMINE HYDROCHLORIDE 50 mg/1 1
INACTIVE INGREDIENTS: CROSCARMELLOSE SODIUM; DIBASIC CALCIUM PHOSPHATE DIHYDRATE; FD&C BLUE NO. 1; MAGNESIUM STEARATE; MICROCRYSTALLINE CELLULOSE; POLYETHYLENE GLYCOLS; POLYVINYL ALCOHOL, UNSPECIFIED; SILICON DIOXIDE; STEARIC ACID; TALC; TITANIUM DIOXIDE; FERRIC OXIDE YELLOW

Somnapure Clinical Strength

Drug Facts

Active ingredient (in each caplet)

Diphenhydramine HCl 50 mg

Purpose

Nighttime sleep aid

INDICATIONS AND USAGE

Use for relief of occasional sleeplessness

Warnings

Do not use

- in children under 12 years of age
- with any other product containing diphenhydramine, even one used on skin

Ask a doctor before use if you have

- a breathing problem such as emphysema or chronic bronchitis
- glaucoma
- difficulty in urination due to enlargement of the prostate gland

Ask a doctor before use if you are taking sedatives, tranquilizers, or any other sleep aid.

When using this product, avoid alcoholic drinks.

Stop use and ask a doctor if sleeplessness persists continuously for more than two weeks. Insomnia may be a symptom of a serious underlying medical illness.

PREGNANCY OR BREAST FEEDING

If pregnant or breastfeeding, ask a health professional before use.

Keep out of reach of children. In case of overdose, get medical help or contact a poison control center right away.

Directions

- adults and children 12 years of age and older: 1 caplet (50 mg) at bedtime if needed, or as directed by a doctor

Other information

- each caplet contains: calcium 50 mg
- store at 15°-30°C (59°-86°F)

INACTIVE INGREDIENT

Inactive ingredients croscarmellose sodium, dibasic calcium phosphate dihydrate, FD&C blue #1 aluminum lake, magnesiu stearate, microcrystalline cellulose, polyethylene glycol, polyvinyl alcohol, silcon dioxide, stearic acid, talc, titanium dioxide, yellow iron oxide

Questions of comments? Call 1-855-606-6507

PACKAGE LABEL

Peak Life Somnapure

Clinical Strength

Nighttime Sleep Aid / Diphenhydramine HCl

#1 Doctor-Recommended Ingredient

- Fall Asleep Quickly
- Wake Up Energized
- Non-Habit-Forming

30 Sleep Caplets

One Caplet per Dose

LNK Carton